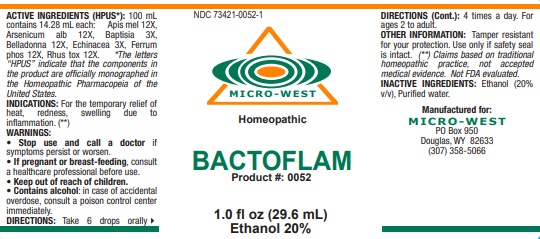 DRUG LABEL: BACTOFLAM
NDC: 73421-0052 | Form: LIQUID
Manufacturer: White Manufacturing Inc. DBA Micro-West
Category: homeopathic | Type: HUMAN OTC DRUG LABEL
Date: 20221202

ACTIVE INGREDIENTS: APIS MELLIFERA 12 [hp_X]/29.6 mL; ARSENIC TRIOXIDE 12 [hp_X]/29.6 mL; BAPTISIA TINCTORIA ROOT 3 [hp_X]/29.6 mL; ATROPA BELLADONNA 12 [hp_X]/29.6 mL; ECHINACEA, UNSPECIFIED 3 [hp_X]/29.6 mL; FERROSOFERRIC PHOSPHATE 12 [hp_X]/29.6 mL; TOXICODENDRON PUBESCENS LEAF 12 [hp_X]/29.6 mL
INACTIVE INGREDIENTS: ALCOHOL; WATER

BACTOFLAM

ACTIVE INGREDIENT

ACTIVE INGREDIENTS (HPUS*): 100 mL contains 14.28 mL each: Apis mel 12X, Arsenicum alb 12X, Baptisia 3X,
Belladonna 12X, Echinacea 3X, Ferrum phos 12X, Rhus tox 12X.

*The letters “HPUS” indicate that the components in the product are officially monographed in the Homeopathic Pharmacopeia of the
United States

Claims based on traditional homeopathic practice, not accepted medical evidence. Not FDA evaluated.

INDICATIONS AND USAGE

INDICATIONS: For the temporary relief of heat, redness, swelling due to inflammation. (**)

WARNINGS:
• Stop use and call a doctor if symptoms persist or worsen.
• If pregnant or breast-feeding, consult a healthcare professional before use.
• Keep out of reach of children.
• Contains alcohol: in case of accidental overdose, consult a poison control center
immediately.

- Keep out of reach of children.

DOSAGE AND ADMINISTRATION

DIRECTIONS: Take 6 drops orally 4 times a day. For ages 2 to adult.

OTHER INFORMATION: Tamper resistant for your protection. Use only if safety seal is intact.

INACTIVE INGREDIENTS: Ethanol (20% v/v), Purified water.

QUESTIONS

Manufactured for:
MICRO-WEST
PO Box 950
Douglas, WY 82633
(307) 358-5066

PACKAGE LABEL

NDC 73421-0052-1

MICRO-WEST

Homeopathic

BACTOFLAM

Product #: 0052

1.0 fl oz (29.6 mL)

Ethanol 20%

PURPOSE

For the temporary relief of heat, redness, swelling due to inflammation.